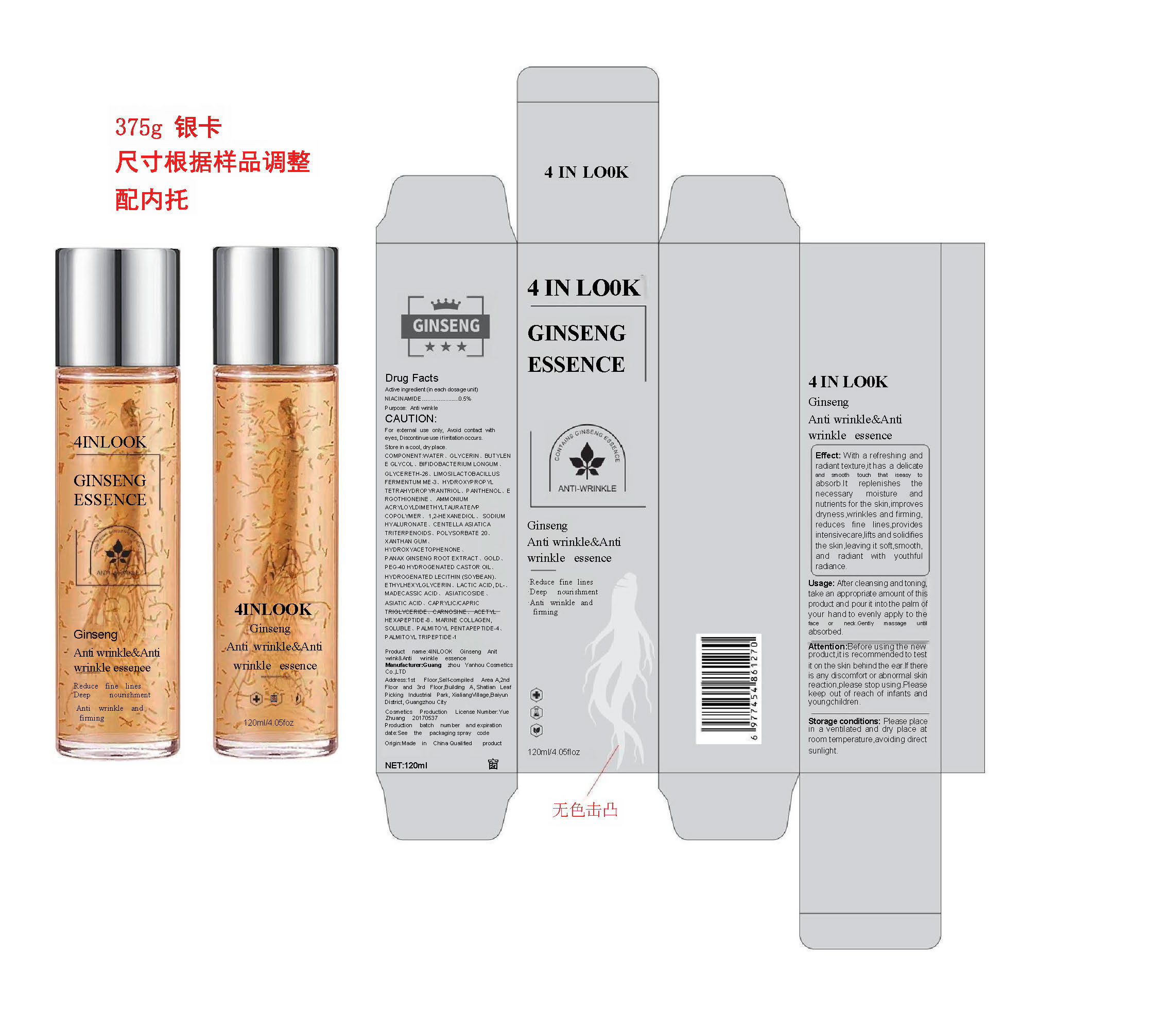 DRUG LABEL: 4 IN LOOK Ginseng Anit wrink Anti wrinkle essence
NDC: 85977-001 | Form: EMULSION
Manufacturer: Guangzhou Yanhou Cosmetics Co., Ltd.
Category: otc | Type: HUMAN OTC DRUG LABEL
Date: 20250729

ACTIVE INGREDIENTS: NIACINAMIDE 0.5 g/100 mL
INACTIVE INGREDIENTS: ASIATICOSIDE; POLYSORBATE 20; BIFIDOBACTERIUM LONGUM; MADECASSIC ACID; HYDROGENATED SOYBEAN LECITHIN; BUTYLENE GLYCOL; AMMONIUM ACRYLOYLDIMETHYLTAURATE/VP COPOLYMER; 1,2-HEXANEDIOL; GLYCERETH-26; PANAX GINSENG ROOT; PEG-40 HYDROGENATED CASTOR OIL; ETHYLHEXYLGLYCERIN; ASIATIC ACID; CARNOSINE; PALMITOYL PENTAPEPTIDE-4; LACTIC ACID, DL-; GLYCERIN; WATER; HYDROXYPROPYL TETRAHYDROPYRANTRIOL; CENTELLA ASIATICA TRITERPENOIDS; HYDROXYACETOPHENONE; ERGOTHIONEINE; LIMOSILACTOBACILLUS FERMENTUM ME-3; MARINE COLLAGEN, SOLUBLE; XANTHAN GUM; ACETYL HEXAPEPTIDE-8; PALMITOYL TRIPEPTIDE-1; GOLD; CAPRYLIC/CAPRIC TRIGLYCERIDE; PANTHENOL; SODIUM HYALURONATE

85977-001 4 IN LOOK Ginseng Anit wrink&Anti wrinkle essence

ACTIVE INGREDIENT

NIACINAMIDE 0.5%

PURPOSE

Anti winkle

INDICATIONS AND USAGE

Effect: with a refreshing andradiant texture,it has a delicatetouch thatiseasy toandst oothabsorb .ltreplenishesthenecessanmoistureandnutrients for the skin,improvesdryness ,wrinkles and firming.reduces fine lines,providesintensivecare,lifts and solidifiesthe skin leaving it soft,smooth.and radiant with youthfulradiance

WARNINGS

For exernal use only,Awoid contact witheyes, Discontinue use ifiritation occursStore in a cool, dry place

WHEN USING

Before using the newproductitis recommended to testit on the skin behind the ear lf thereis any discomfort or abnormal skinreaction,please stop using.Pleasekeep out of reach of infants andyoungchildren.

STOP USE

Before using the newproductitis recommended to testit on the skin behind the ear lf thereis any discomfort or abnormal skinreaction,please stop using.

Pleasekeep out of reach of infants andyoungchildren.

DOSAGE AND ADMINISTRATION

Usage: After cleansing and toningtake an appropriate amount of thisproduct and pour it into the palm ofyour hand to evenly apply to the face or neck .Gently massage until absorbed

INACTIVE INGREDIENT

WATER
GLYCERIN
BUTYLENE GLYCOL
BIFIDOBACTERIUM LONGUM
GLYCERETH-26
LIMOSILACTOBACILLUS FERMENTUM ME-3
HYDROXYPROPYL TETRAHYDROPYRANTRIOL
PANTHENOL
ERGOTHIONEINE
AMMONIUM ACRYLOYLDIMETHYLTAURATE/VP COPOLYMER
1,2-HEXANEDIOL
SODIUM HYALURONATE
CENTELLA ASIATICA TRITERPENOIDS
POLYSORBATE 20
XANTHAN GUM
HYDROXYACETOPHENONE
PANAX GINSENG ROOT EXTRACT
GOLD
PEG-40 HYDROGENATED CASTOR OIL
HYDROGENATED LECITHIN (SOYBEAN)
ETHYLHEXYLGLYCERIN
LACTIC ACID, DL-
MADECASSIC ACID
ASIATICOSIDE
ASIATIC ACID
CAPRYLIC/CAPRIC TRIGLYCERIDE
CARNOSINE
ACETYL HEXAPEPTIDE-8
MARINE COLLAGEN, SOLUBLE
PALMITOYL PENTAPEPTIDE-4
PALMITOYL TRIPEPTIDE-1